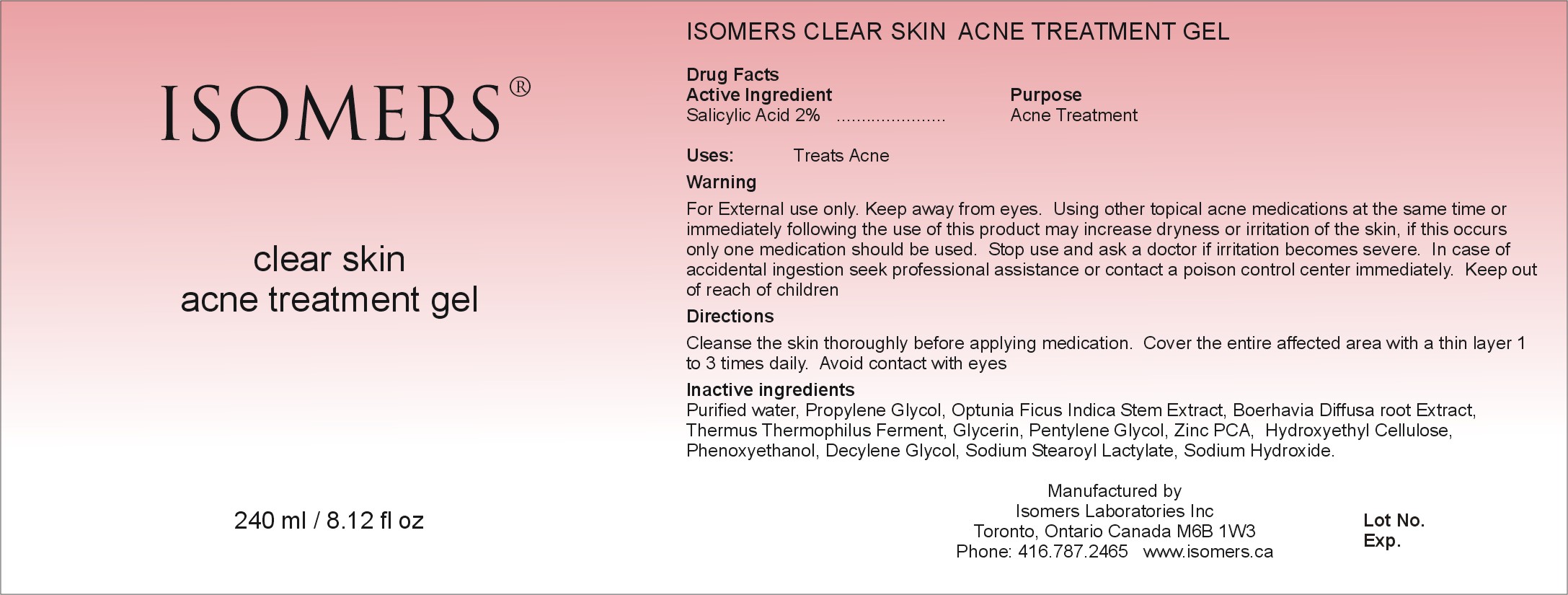 DRUG LABEL: Isomers Clear Skin Acne Treatment Gel
NDC: 64990-601 | Form: GEL
Manufacturer: Isomers Laboratories Inc
Category: otc | Type: HUMAN OTC DRUG LABEL
Date: 20100217

ACTIVE INGREDIENTS: SALICYLIC ACID 0.02 mL/1 mL
INACTIVE INGREDIENTS: WATER; PROPYLENE GLYCOL; OPUNTIA FICUS-INDICA; GLYCERIN; HYDROXYETHYL CELLULOSE (2000 CPS AT 1%); PHENOXYETHANOL; SODIUM HYDROXIDE

DRUG FACTS

ACTIVE INGREDIENT

Enter section text here

ACTIVE INGREDIENT

SALICYLIC ACID 2%

PURPOSE

Enter section text here

PURPOSE

ACNE TREATMENT

ASK DOCTOR

Enter section text here

STOP USE AND ASK DOCTOR

IF IRRITATION BECOMES SEVERE

KEEP OUT OF REACH OF CHILDREN

Enter section text here

KEEP OUT OF REACH OF CHILDREN

WARNINGS

Enter section text here

WARNING:

- FOR EXTERNAL USE ONLY
- KEEP AWAY FROM EYES
- Using other topical acne medications at the same time or immediately following the use of this product may increase dryness or irritation of the skin, if this occurs only one medication should be used.
- In case of accidental ingestion seek professional assistance or contact a poison control center immediately.

INACTIVE INGREDIENT

Enter section text here

INACTIVE INGREDIENTS:

Purified water, Propylene Glycol, Optunia Ficus Indica Stem Extract, Boerhavia Diffusa root Extract, Thermus Thermophilus Ferment, Glycerin, Pentylene Glycol, Zinc PCA,, Hydroxyethyl Cellulose, Phenoxyethanol, Decylene Glycol, Sodium Stearoyl Lactylate, Sodium Hydroxide.

PACKAGE LABEL

CSATG240.jpg